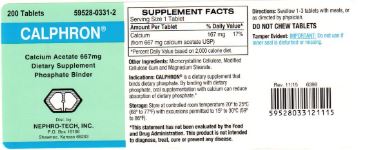 DRUG LABEL: Calphron
NDC: 59528-0331 | Form: TABLET
Manufacturer: Nephro-Tech, Inc.
Category: other | Type: DIETARY SUPPLEMENT
Date: 20160512

ACTIVE INGREDIENTS: CALCIUM ACETATE 667 mg/1 1

Calphron (calcium acetate)

Principal Display Panel

59528-0331-2

Calphron

Dietary Supplement

Phosphate Binder

200 Tablets

Directions

Swallow 1-3 tablets with meals, or as directed by physician.

Dietary Supplement Phosphate Binder

Calphron is a dietary supplement that binds dietary phosphate. By binding with dietary phosphate, oral supplementation with calcium can reduce absorption of dietary phosphate.*

*This statement has not been evaluated by the Food and Drug Administration. This product is not intended to diagnose, treat, cure or prevent any disease.